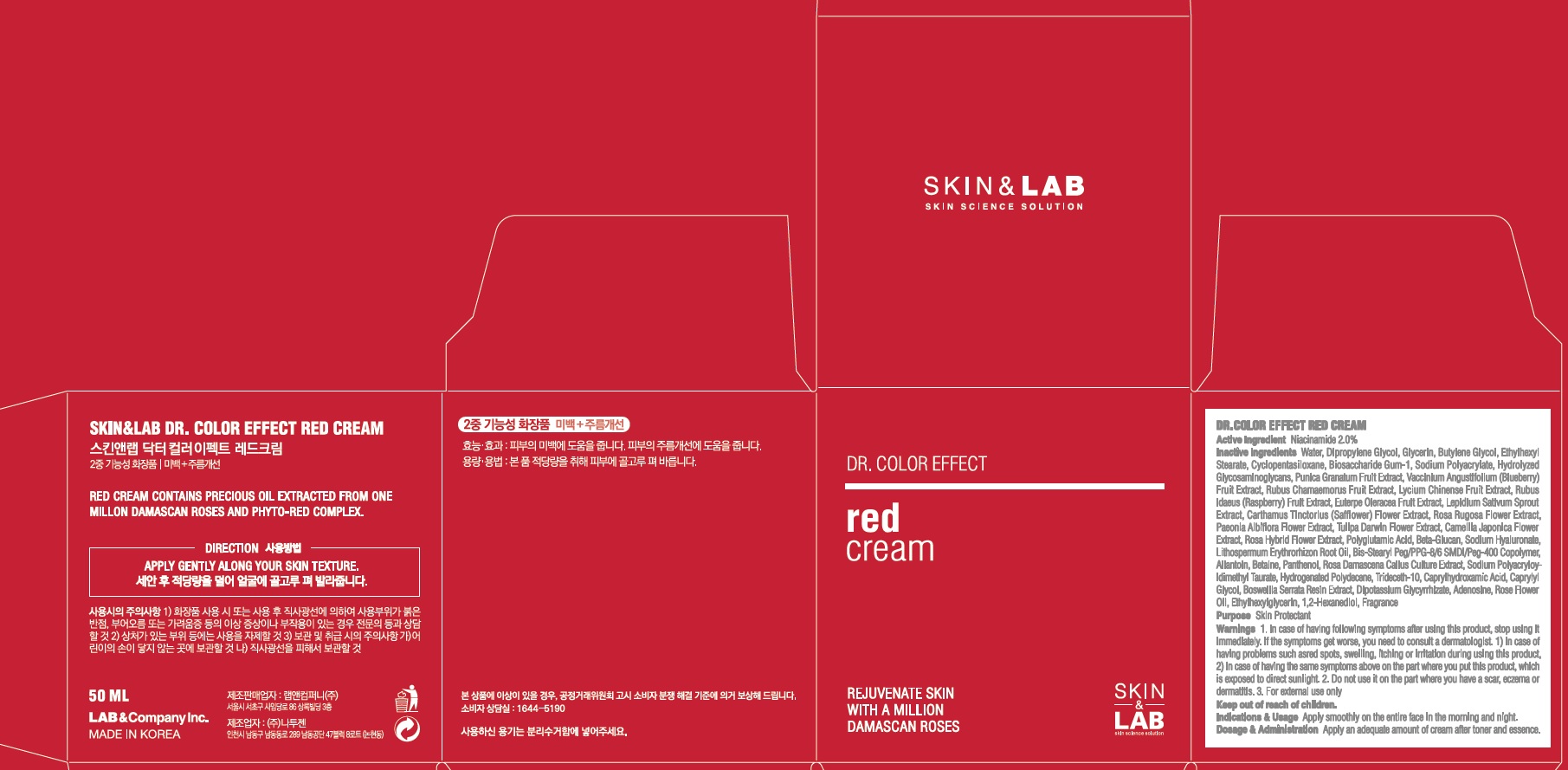 DRUG LABEL: DR. COLOR EFFECT RED
NDC: 69457-020 | Form: CREAM
Manufacturer: LAB & Company Inc.
Category: otc | Type: HUMAN OTC DRUG LABEL
Date: 20180515

ACTIVE INGREDIENTS: Niacinamide 1.0 g/50 mL
INACTIVE INGREDIENTS: Water; Dipropylene Glycol

ACTIVE INGREDIENT

Active Ingredient: Niacinamide 2.0%

INACTIVE INGREDIENT

Inactive Ingredients:

Water, Dipropylene Glycol, Glycerin, Butylene Glycol, Ethylhexyl Stearate, Cyclopentasiloxane, Biosaccharide Gum-1, Sodium Polyacrylate, Hydrolyzed Glycosaminoglycans, Punica Granatum Fruit Extract, Vaccinium Angustifolium (Blueberry) Fruit Extract, Rubus Chamaemorus Fruit Extract, Lycium Chinense Fruit Extract, Rubus Idaeus (Raspberry) Fruit Extract, Euterpe Oleracea Fruit Extract, Lepidium Sativum Sprout Extract, Carthamus Tinctorius (Safflower) Flower Extract, Rosa Rugosa Flower Extract, Paeonia Albiflora Flower Extract, Tulipa Darwin Flower Extract, Camellia Japonica Flower Extract, Rosa Hybrid Flower Extract, Polyglutamic Acid, Beta-Glucan, Sodium Hyaluronate, Lithospermum Erythrorhizon Root Oil, Bis-Stearyl Peg/PPG-8/6 SMDI/Peg-400 Copolymer, Allantoin, Betaine, Panthenol, Rosa Damascena Callus Culture Extract, Sodium Polyacryloyldimethyl Taurate, Hydrogenated Polydecene, Trideceth-10, Caprylhydroxamic Acid, Caprylyl Glycol, Boswellia Serrata Resin Extract, Dipotassium Glycyrrhizate, Adenosine, Rose Flower Oil, Ethylhexylglycerin, 1,2-Hexanediol, Fragrance

PURPOSE

Purpose: Skin Protectant

WARNINGS

Warnings: 1. In case of having following symptoms after using this product, stop using it immediately. If the symptoms get worse, you need to consult a dermatologist. 1) In case of having problems such as red spots, swelling, itching or irritation during using this product, 2) In case of having the same symptoms above on the part where you put this product, which is exposed to direct sunlight. 2. Do not use it on the part where you have a scar, eczema or dermatitis. 3. For external use only

Keep out of reach of children: Keep out of reach of babies and children

INDICATIONS & USAGE

Indications & Usage: Apply smoothly on the entire face in the morning and night.

DOSAGE & ADMINISTRATION

Dosage & Administration: Take an adequate amount of this product after toner and essence. To feel stronger effect, please use it with RED SERUM